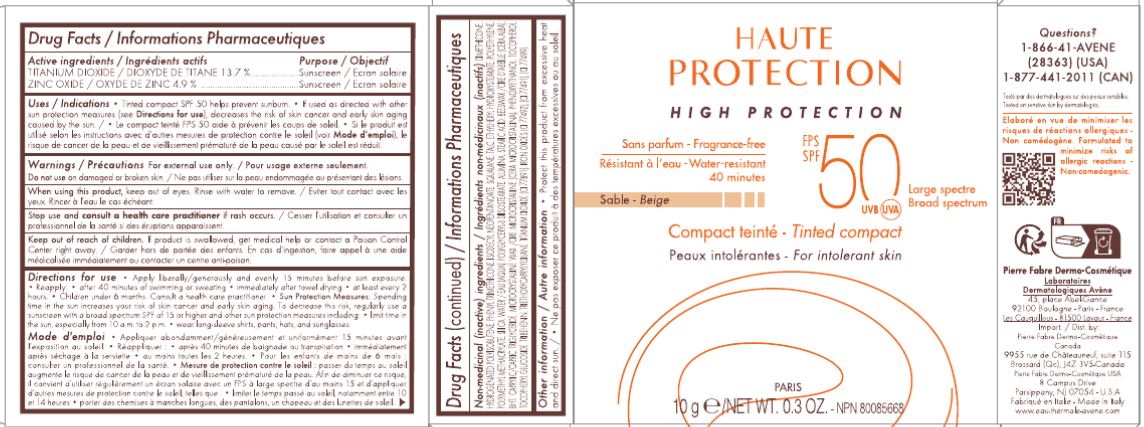 DRUG LABEL: HAUTE PROTECTION High Protection Tinted Compact Broad Spectrum SPF 50 Beige
NDC: 67015-2036 | Form: CREAM
Manufacturer: Pierre Fabre USA Inc.
Category: otc | Type: HUMAN OTC DRUG LABEL
Date: 20240129

ACTIVE INGREDIENTS: ZINC OXIDE 4.9 g/100 g; TITANIUM DIOXIDE 13.7 g/100 g
INACTIVE INGREDIENTS: WATER; FERRIC OXIDE YELLOW; FERROSOFERRIC OXIDE; FERRIC OXYHYDROXIDE; HYDROGENATED POLYBUTENE (1300 MW); FERRIC OXIDE RED; MEDIUM-CHAIN TRIGLYCERIDES; BUTYLATED HYDROXYTOLUENE; TRIETHOXYCAPRYLYLSILANE; TRIBEHENIN; MICROCRYSTALLINE WAX; ALUMINUM OXIDE; POLY(METHYL METHACRYLATE; 450000 MW); SQUALANE; TOCOPHEROL; PHENOXYETHANOL; YELLOW WAX; SILICON DIOXIDE; HIGH DENSITY POLYETHYLENE; TALC; ISODECYL NEOPENTANOATE; PHENYL TRIMETHICONE; DIMETHICONE; POLYGLYCERYL-3 DIISOSTEARATE; ETHYLHEXYL HYDROXYSTEARATE; STEARIC ACID

HAUTE PROTECTION High Protection Tinted Compact Broad Spectrum SPF 50

Active ingredients

TITANIUM DIOXIDE 13.7 %
ZINC OXIDE 4.9 %

Purpose

Sunscreen

Uses

- Tinted compact SPF 50 helps prevent sunburn.
- If used as directed with other sun protection measures (see Directions for use), decreases the risk if skin cancer and early skin aging caused by the sun.

Warnings

For external use only

Do not use on damaged or broken skin.

When using this product, keep out of eyes. Rinse with water to remove.

Stop use and consult a health care practitioner if rash occurs.

Keep out of reach of children.

If product is swallowed, get medical help or contact a Poison Control Center right away.

Directions for use

- Apply liberally/generously and evenly15 minutes before sun exposure.
- Reapply:
- after 40 minutes of swimming or sweating
- immediately after towel drying
- at least every 2 hours.
- Children under 6 months: Consult a health care practitioner.
- Sun Protection Measures: Spending time in the sun increases your risk of skin cancer and early skin aging. To decrease this risk, regularly use a sunscreen with a Broad Spectrum SPF of 15 or higher and other skin protection measures including:
- limit time in the sun, especially from 10 a.m. - 2 p.m.
- wear long-sleeve shirts, pants, hats and sunglasses.

Inactive Ingredients

DIMETHICONE, HYDROGENATED POLYISOBUTENE, PHENYL TRIMETHICONE, ISODECYL NEOPENTANOATE, SQUALANE, TALC, ETHYLHEXYL HYDROXYSTEARATE, POLYETHYLENE, POLYMETHYL METHACRYLATE, SILICA, WATER/EAU, POLYGLYCERLYL-3 DIISOSTEARATE, ALUMINA, STEARIC ACID, BEESWAX, BHT, CAPRYLIC/CAPRIC TRIGLYCERIDE, MICROCRYSTALLINE WAX, PHENOXYETHANOL, TOCOPHEROL, TOCOPHERYL GLUCOSIDE, TRIBEHENIN, TRIETHOXYCAPRYLYLSILANE, TITANIUM DIOXIDE (CI77891), IRON OXIDES (CI77492), (CI77491), (CI77499)

Other Information

Protect this product from excessive heat and direct sun.

HAUTE PROTECTION High Protection Tinted Compact Broad Spectrum SPF 50 BEIGE 10g (67015-2036-0)

HAUTE

PROTECTION

HIGH PROTECTION

Fragrance-free

SPF 50 UVB UVA Broad spectrum

Water-resistant

40 minutes

Beige

Tinted compact

For intolerant skin

PARIS

10g e/NET WT. 0.3 OZ.- NPN80085668